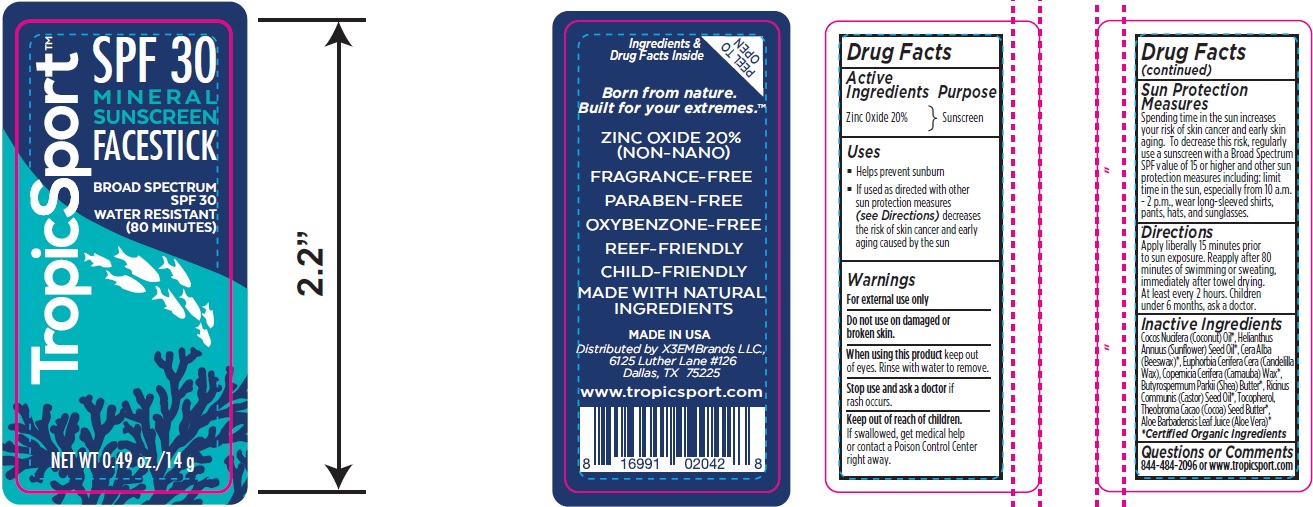 DRUG LABEL: SUNSCREEN
NDC: 62932-183 | Form: OINTMENT
Manufacturer: Private Label Select Ltd CO
Category: otc | Type: HUMAN OTC DRUG LABEL
Date: 20181123

ACTIVE INGREDIENTS: ZINC OXIDE 14 g/100 g
INACTIVE INGREDIENTS: CASTOR OIL; TOCOPHEROL; ALOE VERA LEAF; YELLOW WAX; COCOA BUTTER; COCONUT OIL; HELIANTHUS ANNUUS SEED WAX; CANDELILLA WAX; CARNAUBA WAX; SHEA BUTTER

X3EM Tropicsport Mineral Sunscreen Facestick SPF30